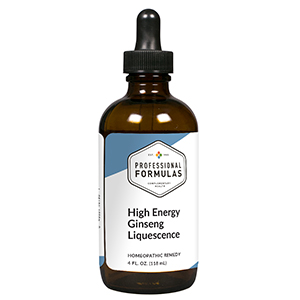 DRUG LABEL: High Energy Ginseng Liquescence
NDC: 63083-3032 | Form: LIQUID
Manufacturer: Professional Complementary Health Formulas
Category: homeopathic | Type: HUMAN OTC DRUG LABEL
Date: 20190815

ACTIVE INGREDIENTS: PANAX QUINQUEFOLIUS WHOLE 1 [hp_X]/118 mL; ASIAN GINSENG 1 [hp_X]/118 mL; ELEUTHEROCOCCUS SENTICOSUS STEM 1 [hp_X]/118 mL
INACTIVE INGREDIENTS: ALCOHOL; WATER

T32

ACTIVE INGREDIENTS

Panax quinquefolius (American ginseng) 1X, 3X, 6X, 12X
Panax ginseng (Korean) 1X, 3X, 6X, 12X
Panax ginseng (Chinese red) 1X, 3X, 6X, 12X
Eleutherococcus senticosus (Siberian) 1X, 3X, 6X, 12X

QUESTIONS

Professional Formulas

PO Box 2034 Lake Oswego, OR 97035

INDICATIONS

For the temporary relief of reduced strength, energy, or stamina.*

PURPOSE

*Claims based on traditional homeopathic practice, not accepted medical evidence. Not FDA evaluated.

WARNINGS

In case of overdose, get medical help or contact a poison control center right away.

Keep out of the reach of children.

PREGNANCY OR BREAST FEEDING

If pregnant or breastfeeding, ask a healthcare professional before use.

DIRECTIONS

Place drops under tongue 30 minutes before/after meals. Adults and children 12 years and over: Take one full dropper up to 2 times per day. Consult a physician for use in children under 12 years of age.

OTHER INFORMATION

Tamper resistant. If seal is broken, do not use. After opening, close container tightly and store at room temperature away from heat.

INACTIVE INGREDIENTS

20% ethanol, purified water.

LABEL

Est 1985

Professional Formulas

Complementary Health

High Energy Ginseng Liquescence

Homeopathic Remedy

4 FL. OZ. (118 mL)